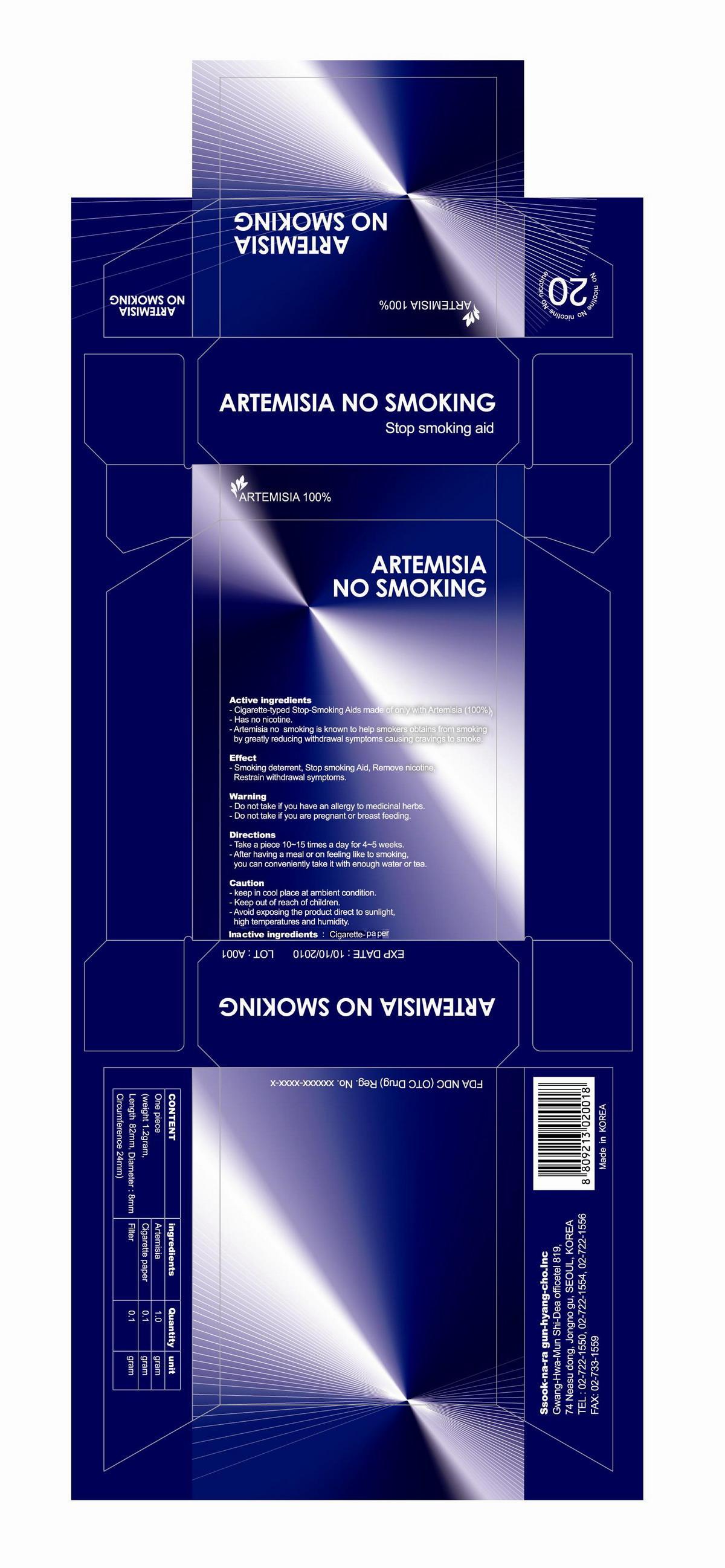 DRUG LABEL: Artemisia No Smoking
NDC: 51978-1001 | Form: INHALANT
Manufacturer: Donghwa Pharm Co., Ltd
Category: otc | Type: HUMAN OTC DRUG LABEL
Date: 20140110

ACTIVE INGREDIENTS: WORMWOOD 1 g/1 g
INACTIVE INGREDIENTS: FLATHEAD SOLE

Drug Facts

Active ingredient: Artemisia

DESCRIPTION

Cigarette-typed Stop-Smoking Aids made of only with Artemisia (100%)
Has no nicotine.
Artemisia no smoking is known to help smokers obtains from smoking by greatly reducing withdrawal symptoms causing cravings to smoke

WHEN USING

Usage
- Beneficial to health of smokers
- helpful to those who want to stop smoking
- provides effect of artemisia to ordinary prople as a well-being product

PURPOSE

Usage
· Beneficial to health of smokers
· Helpful to those who want to stop smoking
· Provides effect of Artemisia moxacautery to ordinary people as a well-being product

KEEP OUT OF REACH OF CHILDREN

Caution
ü keep in cool place at ambient condition.
ü Keep out of reach of children.
ü Avoid exposing the product direct to sunlight, high temperatures and humidity

Usage
· Beneficial to health of smokers
· Helpful to those who want to stop smoking
· Provides effect of Artemisia moxacautery to ordinary people as a well-being product

Warning
ü Do not take if you have an allergy to medicinal herbs.
ü Do not take if you are pregnant or breast feeding

Directions
ü Take a piece 10~15 times a day for 4~5 weeks.
ü After having a meal or on feeling like to smoking, you can conveniently take it with enough water or tea

Inactive ingredient: Flathead Sole